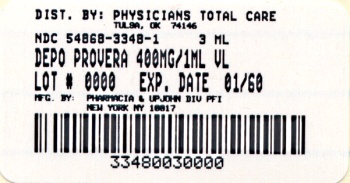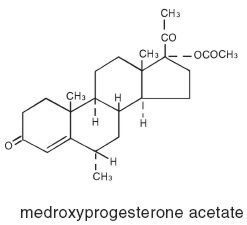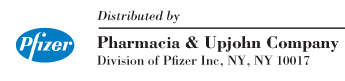 DRUG LABEL: Depo-Provera
NDC: 54868-3348 | Form: INJECTION, SUSPENSION
Manufacturer: Physicians Total Care, Inc.
Category: prescription | Type: HUMAN PRESCRIPTION DRUG LABEL
Date: 20090812

ACTIVE INGREDIENTS: MEDROXYPROGESTERONE ACETATE 400 mg/1 mL
INACTIVE INGREDIENTS: POLYETHYLENE GLYCOL 3350 20.3 mg/1 mL; SODIUM SULFATE ANHYDROUS 11 mg/1 mL; SODIUM HYDROXIDE; HYDROCHLORIC ACID

Depo-Provera®
medroxyprogesterone
acetate injectable
suspension, USP

DESCRIPTION

DEPO-PROVERA Sterile Aqueous Suspension contains medroxyprogesterone acetate, which is a derivative of progesterone and is active by the parenteral and oral routes of administration. It is a white to off-white, odorless crystalline powder, stable in air, melting between 200° and 210° C. It is freely soluble in chloroform, soluble in acetone and in dioxane, sparingly soluble in alcohol and methanol, slightly soluble in ether and insoluble in water.

The chemical name for medroxyprogesterone acetate is Pregn-4-ene-3,20-dione, 17-(acetyloxy)-6-methyl-, (6α)-. The structural formula is:

DEPO-PROVERA for intramuscular injection is available as 400 mg/mL medroxyprogesterone acetate. Each mL of the 400 mg/mL suspension contains:

Medroxyprogesterone acetate .............400 mg
Polyethylene glycol 3350.....................20.3 mg
Sodium sulfate anhydrous ......................11 mg
with
Myristyl-gamma-picolinium
chloride ............................................1.69 mg
added as preservative

When necessary, pH was adjusted with sodium hydroxide and/or hydrochloric acid.

ACTIONS

Medroxyprogesterone acetate, administered parenterally in the recommended doses to women with adequate endogenous estrogen, transforms proliferative endometrium into secretory endometrium.

Medroxyprogesterone acetate inhibits (in the usual dose range) the secretion of pituitary gonadotropin which, in turn, prevents follicular maturation and ovulation.

Because of its prolonged action and the resulting difficulty in predicting the time of withdrawal bleeding following injection, medroxyprogesterone acetate is not recommended in secondary amenorrhea or dysfunctional uterine bleeding. In these conditions oral therapy is recommended.

INDICATIONS AND USES

Adjunctive therapy and palliative treatment of inoperable, recurrent, and metastatic endometrial or renal carcinoma.

CONTRAINDICATIONS

1. Known or suspected pregnancy or as a diagnostic test for pregnancy
2. Undiagnosed vaginal bleeding
3. Known or suspected malignancy of breast
4. Active thrombophlebitis, or current or past history of thromboembolic disorders, or cerebral vascular disease
5. Liver dysfunction or disease
6. Known sensitivity to DEPO-PROVERA (medroxyprogesterone acetate or any of its other ingredients).

WARNINGS

1. Pregnancy

The use of progestational drugs during the first four months of pregnancy is not recommended. Progestational agents have been used beginning with the first trimester of pregnancy in attempts to prevent abortion but there is no evidence that such use is effective. Furthermore, the use of progestational agents, with their uterine-relaxant properties, in patients with fertilized defective ova may cause a delay in spontaneous abortion.

2. Intrauterine Exposure

Several reports suggest an association between intrauterine exposure to progestational drugs in the first trimester of pregnancy and genital abnormalities in male and female fetuses. The risk of hypospadias (5 to 8 per 1,000 male births in the general population) may be approximately doubled with exposure to these drugs. There are insufficient data to quantify the risk to exposed female fetuses, but insofar as some of these drugs induce mild virilization of the external genitalia of the female fetus, and because of the increased association of hypospadias in the male fetus, it is prudent to avoid the use of these drugs during the first trimester of pregnancy.

If the patient is exposed to DEPO-PROVERA Sterile Aqueous Suspension during the first four months of pregnancy or if she becomes pregnant while taking this drug, she should be apprised of the potential risks to the fetus.

3. Thromboembolic Disorders

The physician should be alert to the earliest manifestations of thrombotic disorder (thrombophlebitis, cerebrovascular disorder, pulmonary embolism, and retinal thrombosis). Should any of these occur or be suspected, the drug should be discontinued immediately.

4. Ocular Disorders

Medication should be discontinued pending examination if there is a sudden partial or complete loss of vision, or if there is a sudden onset of proptosis, diplopia or migraine. If examination reveals papilledema or retinal vascular lesions, medication should be withdrawn.

5. Lactation

Detectable amounts of drug have been identified in the milk of mothers receiving progestational drugs. The effect of this on the nursing infant has not been determined.

6. Multi-dose Use

Multi-dose use of DEPOPROVERA Sterile Aqueous Suspension from a single vial requires special care to avoid contamination. Although initially sterile, any multi-dose use of vials may lead to contamination unless strict aseptic technique is observed.

PRECAUTIONS

1. Physical Examination

It is good medical practice for all women to have annual history and physical examinations, including women using DEPO-PROVERA Sterile Aqueous Suspension. The physical examination, however, may be deferred until after initiation of DEPO-PROVERA if requested by the woman and judged appropriate by the clinician. The physical examination should include special reference to blood pressure, breasts, abdomen and pelvic organs, including cervical cytology and relevant laboratory tests. In case of undiagnosed, persistent or recurrent abnormal vaginal bleeding, appropriate measures should be conducted to rule out malignancy. Women with a strong family history of breast cancer or who have breast nodules should be monitored with particular care.

2. Fluid Retention

Because progestational drugs may cause some degree of fluid retention, conditions which might be influenced by this condition, such as epilepsy, migraine, asthma, cardiac or renal dysfunction, require careful observation.

3. Vaginal Bleeding

In cases of breakthrough bleeding, as in all cases of irregular bleeding per vaginum, nonfunctional causes should be borne in mind and adequate diagnostic measures undertaken.

4. Depression

Patients who have a history of psychic depression should be carefully observed and the drug discontinued if the depression recurs to a serious degree.

5. Masking of Climacteric

The age of the patient constitutes no absolute limiting factor although treatment with progestin may mask the onset of the climacteric.

6. Use with Estrogen

Studies of the addition of a progestin product to an estrogen replacement regimen for seven or more days of a cycle of estrogen administration have reported a lowered incidence of endometrial hyperplasia. Morphological and biochemical studies of endometrial suggest that 10–13 days of a progestin are needed to provide maximal maturation of the endometrium and to eliminate any hyperplastic changes. Whether this will provide protection from endometrial carcinoma has not been clearly established.

There are possible risks which may be associated with the inclusion of progestin in estrogen replacement regimen, including adverse effects on carbohydrate and lipid metabolism. The dosage used may be important in minimizing these adverse effects.

A decrease in glucose tolerance has been observed in a small percentage of patients on estrogen-progestin combination treatment. The mechanism of this decrease is obscure. For this reason, diabetic patients should be carefully observed while receiving such therapy.

7. Prolonged Use

The effect of prolonged use of DEPO-PROVERA Sterile Aqueous Suspension at the recommended doses on pituitary, ovarian, adrenal, hepatic, and uterine function is not known.

8. Multi-dose Use

When multi-dose vials are used, special care to prevent contamination of the contents is essential. There is some evidence that benzalkonium chloride is not an adequate antiseptic for sterilizing DEPO-PROVERA Sterile Aqueous Suspension multi-dose vials. A povidone-iodine solution or similar product is recommended to cleanse the vial top prior to aspiration of contents. (See WARNINGS)

DRUG INTERACTIONS

Aminoglutethimide administered concomitantly with DEPO-PROVERA Sterile Aqueous Suspension may significantly depress the serum concentrations of medroxyprogesterone acetate. DEPO-PROVERA users should be warned of the possibility of decreased efficacy with the use of this or any related drugs.

LABORATORY TEST INTERACTIONS

The pathologist should be advised of progestin therapy when relevant specimens are submitted. The following laboratory tests may be affected by progestins including DEPO-PROVERA Sterile Aqueous Suspension:

a) Plasma and urinary steroid levels are decreased (e.g. progesterone, estradiol, pregnanediol, testosterone, cortisol).
b) Gonadotropin levels are decreased.
c) Sex-hormone binding globulin concentrations are decreased.
d) Protein bound iodine and butanol extractable protein bound iodine may increase. T3 uptake values may decrease.
e) Coagulation test values for prothrombin (Factor II), and Factors VII, VIII, IX, and X may increase.
f) Sulfobromophthalein and other liver function test values may be increased.
g) The effects of medroxyprogesterone acetate on lipid metabolism are inconsistent. Both increases and decreases in total cholesterol, triglycerides, low-density lipoprotein (LDL) cholesterol, and high-density lipoprotein (HDL) cholesterol have been observed in studies.

CARCINOGENESIS, MUTAGENESIS, IMPAIRMENT OF FERTILITY

Long-term intramuscular administration of Medroxyprogesterone acetate (MPA) has been shown to produce mammary tumors in beagle dogs. There is no evidence of a carcinogenic effect associated with the oral administration of MPA to rats and mice. Medroxyprogesterone acetate was not mutagenic in a battery of in vitro or in vivo genetic toxicity assays.

Medroxyprogesterone acetate at high doses is an anti-fertility drug and high doses would be expected to impair fertility until the cessation of treatment.

INFORMATION FOR THE PATIENT

See Patient Information at end of insert.

ADVERSE REACTIONS

–(See WARNINGS for possible adverse effects on the fetus)
–breakthrough bleeding
–spotting
–change in menstrual flow
–amenorrhea
–headache
–nervousness
–dizziness
–edema
–change in weight (increase or decrease)
–changes in cervical erosion and cervical secretions
–cholestatic jaundice, including neonatal jaundice
–breast tenderness and galactorrhea
–skin sensitivity reactions consisting of urticaria, pruritus, edema and generalized rash
–acne, alopecia and hirsutism
–rash (allergic) with and without pruritis
–anaphylactoid reactions and anaphylaxis
–mental depression
–pyrexia
–fatigue
–insomnia
–nausea
–somnolence

In a few instances there have been undesirable sequelae at the site of injection, such as residual lump, change in color of skin, or sterile abscess.

A statistically significant association has been demonstrated between use of estrogen-progestin combination drugs and pulmonary embolism and cerebral thrombosis and embolism. For this reason patients on progestin therapy should be carefully observed. There is also evidence suggestive of an association with neuro-ocular lesions, e.g. retinal thrombosis and optic neuritis.

The following adverse reactions have been observed in patients receiving estrogen-progestin combination drugs:

–rise in blood pressure in susceptible individuals
–premenstrual syndrome
–changes in libido
–changes in appetite
–cystitis-like syndrome
–headache
–nervousness
–fatigue
–backache
–hirsutism
–loss of scalp hair
–erythema multiforma
–erythema nodosum
–hemorrhagic eruption
–itching
–dizziness

The following laboratory results may be altered by the use of estrogen-progestin combination drugs:

–increased sulfobromophthalein retention and other hepatic function tests
–coagulation tests: increase in prothrombin factors VII, VIII, IX, and X
–metyrapone test
–pregnanediol determinations
–thyroid function: increase in PBI, and butanol extractable protein bound iodine and decrease in T3 uptake values

DOSAGE AND ADMINISTRATION

The suspension is intended for intramuscular administration only.

Endometrial or renal carcinoma— doses of 400 mg to 1000 mg of DEPO-PROVERA Sterile Aqueous Suspension per week are recommended initially. If improvement is noted within a few weeks or months and the disease appears stabilized, it may be possible to maintain improvement with as little as 400 mg per month. Medroxyprogesterone acetate is not recommended as primary therapy, but as adjunctive and palliative treatment in advanced inoperable cases including those with recurrent or metastatic disease.

When multi-dose vials are used, special care to prevent contamination of the contents is essential (See WARNINGS).

HOW SUPPLIED

DEPO-PROVERA Sterile Aqueous Suspension is available as 400 mg/mL in 2.5 mL vials NDC 54868-3348-1.

The text of the patient insert for progestational drugs is set forth below.

PATIENT INFORMATION

DEPO-PROVERA Sterile Aqueous Suspension is a progestational drug. The information below is required by the U.S. Food and Drug Administration to be provided to all patients taking such products. This information relates only to the risk to the unborn child associated with use of progestational drugs during pregnancy. For further information on the use, side effects, and other risks associated with this product, ask your doctor.

WARNING FOR WOMEN

Progesterone or progesterone-like drugs have been used to prevent miscarriage in the first few months of pregnancy. No adequate evidence is available to show that they are effective for this purpose. Furthermore, most cases of early miscarriage are due to causes which could not be helped by these drugs.

There is an increased risk of minor birth defects in children whose mothers take this drug during the first 4 months of pregnancy. Several reports suggest an association between mothers who take these drugs in the first trimester of pregnancy and genital abnormalities in male and female babies. The risk to the male baby is the possibility of being born with a condition in which the opening of the penis is on the underside rather than the tip of the penis (hypospadias). Hypospadias occurs in about 5 to 8 per 1000 male births and is about doubled with exposure to these drugs. There is not enough information to quantify the risk to exposed female fetuses, but enlargement of the clitoris and fusion of the labia may occur, although rarely.

Therefore, since drugs of this type may induce mild masculinization of the external genitalia of the female fetus, as well as hypospadias in the male fetus, it is wise to avoid using the drug during the first trimester of pregnancy.

These drugs have been used as a test for pregnancy but such use is no longer considered safe because of possible damage to a developing baby. Also, more rapid methods for testing for pregnancy are now available.

If you take DEPO-PROVERA Sterile Aqueous Suspension and later find you were pregnant when you took it, be sure to discuss this with your doctor as soon as possible.

Rx only

LAB-0143-3.0
May 2006

Relabeling of "Additional" barcode label by:
Physicians Total Care, Inc.
Tulsa, OK 74146

PRINCIPAL DISPLAY PANEL - 2.5 mL Vial Label

2.5 mL Vial
Rx only

Depo-Provera®
medroxyprogesterone acetate
injectable suspension, USP

400 mg/mL